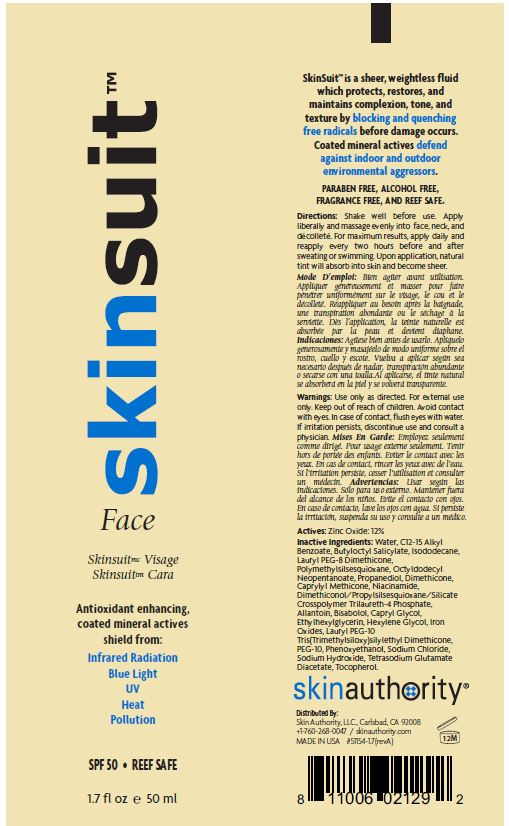 DRUG LABEL: SKINSUIT FACE
NDC: 46007-204 | Form: LOTION
Manufacturer: Skin Authority LLC
Category: otc | Type: HUMAN OTC DRUG LABEL
Date: 20250108

ACTIVE INGREDIENTS: ZINC OXIDE 12 g/100 mL
INACTIVE INGREDIENTS: WATER; ALKYL (C12-15) BENZOATE; BUTYLOCTYL SALICYLATE; ISODODECANE; PEG-8 DIMETHICONE; POLYMETHYLSILSESQUIOXANE (11 MICRONS); OCTYLDODECYL NEOPENTANOATE; PROPANEDIOL; DIMETHICONE; CAPRYLYL TRISILOXANE; NIACINAMIDE; DIMETHICONOL/PROPYLSILSESQUIOXANE/SILICATE CROSSPOLYMER (450000000 MW); TRILAURETH-4 PHOSPHATE; ALLANTOIN; .ALPHA.-BISABOLOL, (+)-; CAPRYLYL GLYCOL; ETHYLHEXYLGLYCERIN; HEXYLENE GLYCOL; FERRIC OXIDE RED; PEG-10 DIMETHICONE (600 CST); POLYETHYLENE GLYCOL 500; PHENOXYETHANOL; SODIUM CHLORIDE; SODIUM HYDROXIDE; TETRASODIUM GLUTAMATE DIACETATE; TOCOPHEROL

Skin Authority - SKINSUIT FACE SPF-50 (46007-204)

ACTIVE INGREDIENT

ZINC OXIDE 12%

PURPOSE

SUNSCREEN

USES

- HELPS PREVENT SUNBURN
- IF USED WITH OTHER SUN PROTECTION MEASURES (SEE DIRECTIONS), DECREASES THE RISK OF SKIN CANCER AND EARLY SKIN AGING CAUSED BY SUN.

WARNINGS

FOR EXTERNAL USE ONLY.

DO NOT USE ON

- BROKEN SKIN
- SERIOUS BURNS

WHEN USING THIS PRODUCT

- KEEP OUT OF EYES. RINSE WITH WATER TO REMOVE.

STOP USE AND ASK A DOCTOR IF

- RASH OR IRRITATION DEVELOPS AND LASTS

KEEP OUT OF REACH OF CHILDREN.

- IF SWALLOWED, GET MEDICAL HELP OR CONTACT A POISON CONTROL CENTER RIGHT AWAY.

SUN PROTECTION MEASURES:

SPENDING TIME IN THE SUN INCREASES YOUR RISK OF SKIN CANCER AND EARLY SKIN AGING. TO DECREASE RISK, REGULARLY USE A SUNSCREEN WITH BROAD SPECTRUM SPF VALUE OF 15+ AND OTHER SUN PROTECTION MEASURES

- LIMIT TIME IN THE SUN FROM 10AM - 2PM
- WEAR LONG SLEEVED SHIRT, PANTS, HATS, AND SUNGLASSES

DIRECTIONS

APPLY EVENLY TO FACE 15 MINUTES BEFORE EXPOSURE.

- REAPPLY EVERY 2 HOURS
- REAPPLY AS NEEDED AFTER SWIMMING OR PERSPIRING
- CHILDREN UNDER 6 MONTHS OF AGE: ASK A DOCTOR

INACTIVE INGREDIENT

WATER, C12-15 ALKYL BENZOATE, BUTYLOCTYL SALICYLATE, ISODODECANSE, LAURYL PEG-8 DIMETHICONE, POLYMETHYLSILSESQUIOXANE, OCTYLDODECYL NEOPENTANOATE, PROPANEDIOL, DIMETHICONE, CAPRYLYL METHICONE, NIACINAMIDE, DIMETHICONOL/PROPYLSILSESQUIOXANE/SILICATE CROSSPOLYMER, TRILAURETH-4 PHOSPHATE, ALLANTOIN, BISABOLOL, CAPRYL GLYCOL, ETHYHEXYLGLYCERIN, HEXYLENE GLYCOL, IRON OXIDES, LAURYL PEG-10 TRIS(TRIMETHYLSILOXY)SILYLETHYL DIMETHICONE, PEG-10, PHENOXYETHANOL, SODIUM CHLORIDE, SODIUM HYDROXIDE, TETRASODIUM GLUTAMATE DIACETATE, TOCOPHEROL.

OTHER INFORMATION

PROTECT THIS PRODUCT FROM EXCESSIVE HEAT AND DIRECT SUN. STORE AT 40° - 95°F (5° - 35°C).

QUESTIONS?

1-866-325-7546

MONDAY - FRIDAY (9 A.M. TO 5 P.M. PST)